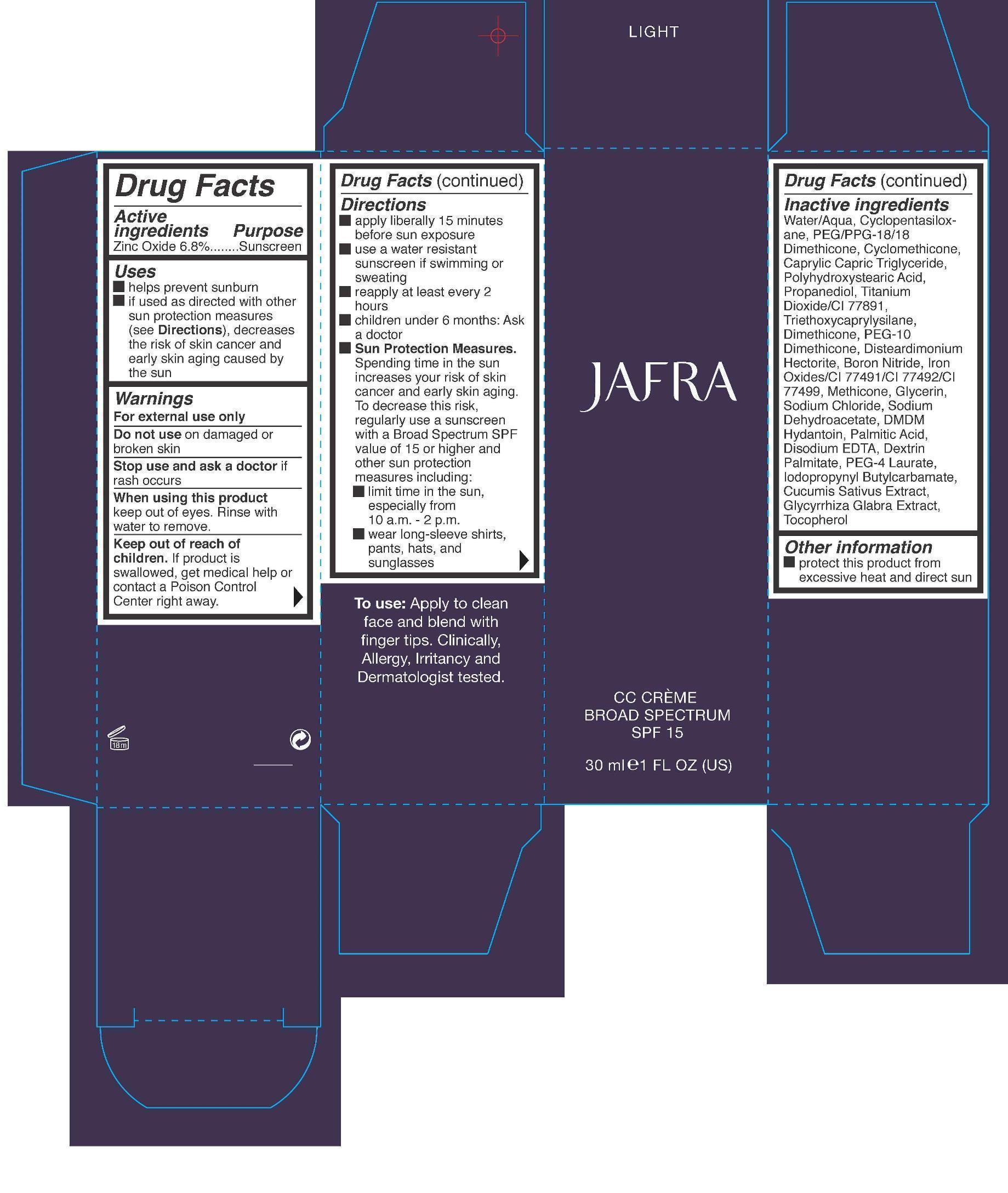 DRUG LABEL: Dark CC creme Broad Spectrum SPF 15
NDC: 68828-237 | Form: CREAM
Manufacturer: Jafra Cosmetics International
Category: otc | Type: HUMAN OTC DRUG LABEL
Date: 20190617

ACTIVE INGREDIENTS: ZINC OXIDE 6.8 g/100 mL
INACTIVE INGREDIENTS: WATER; CYCLOMETHICONE 5; PEG/PPG-18/18 DIMETHICONE; CYCLOMETHICONE; MEDIUM-CHAIN TRIGLYCERIDES; POLYHYDROXYSTEARIC ACID (2300 MW); PROPANEDIOL; TITANIUM DIOXIDE; TRIETHOXYCAPRYLYLSILANE; DIMETHICONE; PEG-10 DIMETHICONE (600 CST); DISTEARDIMONIUM HECTORITE; BORON NITRIDE; FERRIC OXIDE RED; FERRIC OXIDE YELLOW; FERROSOFERRIC OXIDE; METHICONE (20 CST); GLYCERIN; SODIUM CHLORIDE; SODIUM DEHYDROACETATE; DMDM HYDANTOIN; PALMITIC ACID; EDETATE DISODIUM; PEG-4 LAURATE; IODOPROPYNYL BUTYLCARBAMATE; CUCUMBER; GLYCYRRHIZA GLABRA; TOCOPHEROL

Dark CC Creme Broad Spectrum SPF 15

Active

ingredients Purpose

Zinc Oxide 6.8% ......... Sunscreen

Uses

- helps prevent sunburn
- if used as directed with other sun protection measures (see Directions), decreases the risk of skin cancer and early skin aging caused by the sun

Keep out of reach of children. If product is swallowed, get medical help or contact a Poison Control Center right away.

Stop use and ask a doctor if rash occurs

WARNINGS

- For external use only
- Do not use on damaged or broken skin
- When using this productkeep out of eyes. Rinse with water to remove.

Directions

- apply liberally 15 minutes before sun exposure
- use a water resistant sunscreen if swimming of sweating
- reapply at least every 2 hours
- children under 6 months: Ask a doctor
- Sun Protection Measures. Spending time in the sun increases your risk of skin cancer and early skin aging. To decrease this risk, regularyl use a sunscreen with a Broad Spectrum SPF of 15 or higher and other sun protection measures including:
- limit time in the sun, especially from 10 a.m. - 2 p.m.
- wear long-sleeve shirts, pants, hats, and sunglasses

INACTIVE INGREDIENT

Water/Aqua, Cyclopentasiloxane, PEG/PPG-18/18 Dimethicone, Cyclomethicone, Caprylic Capric Triglyceride, Polyhyroxystearic Acid, Propanediol, Titanium Dioxide/CI 77891, Triethoxycaprylysilane, Dimethicone, PEG-10 Dimethicone, Disteardimonium Hectorite, Boron Nitride, Iron Oxides/ CI 77491/CI 77492/CI 77499, Methicone, Glycerin, Sodium Chloride, Sodium Dehydroacetate, DMDM Hydantoin, Palmitic Acid, Disodium EDTA, Dextrin, Palmitate, PEG-4 Laurate, Iodopropynyl Butylcarbamate, Cucumis Sativus Extract, Glycrrhiza Glabra Extract, Tocopherol

PACKAGE LABEL

Dark

Jafra

CC Creme

Broad Spectrum SPF 15

30 ml / 1 FL OZ (US)